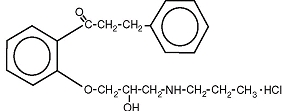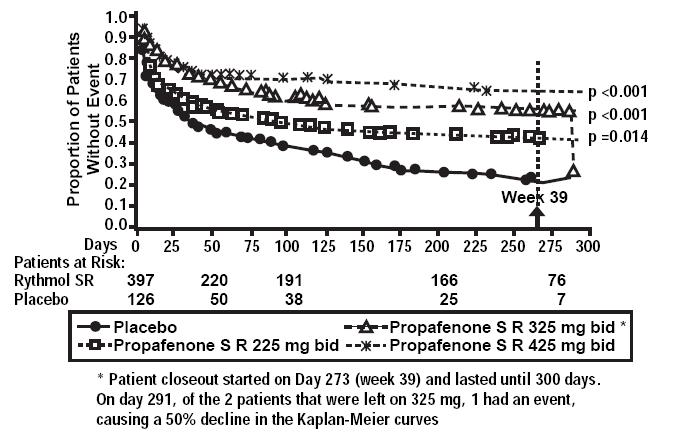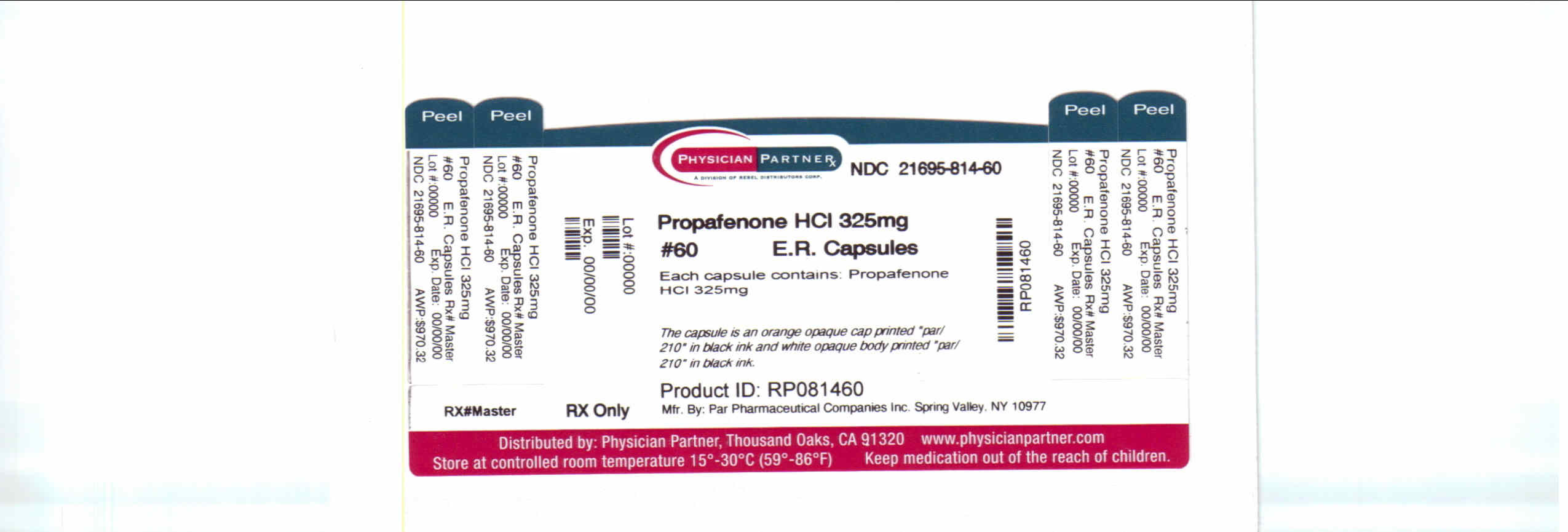 DRUG LABEL: Propafenone
NDC: 21695-814 | Form: CAPSULE, EXTENDED RELEASE
Manufacturer: Rebel Distributors Corp
Category: prescription | Type: HUMAN PRESCRIPTION DRUG LABEL
Date: 20110413

ACTIVE INGREDIENTS: PROPAFENONE 325 mg/1 1
INACTIVE INGREDIENTS: ETHYLCELLULOSES; ANHYDROUS LACTOSE; MAGNESIUM STEARATE; POVIDONE; FD&C BLUE NO. 1; GELATIN; TITANIUM DIOXIDE; D&C YELLOW NO. 10; FERRIC OXIDE BLACK; BUTYL ALCOHOL; PROPYLENE GLYCOL; FD&C BLUE NO. 2; FD&C RED NO. 40; SHELLAC; ALCOHOL; ETHANOL; WATER

PROPAFENONE HYDROCHLORIDE EXTENDED RELEASE CAPSULES

DESCRIPTION

Propafenone hydrochloride is an antiarrhythmic drug supplied in extended-release capsules of 225 mg, 325 mg and 425 mg for oral administration.

The structural formula of propafenone HCl is given below:

Propafenone HCl has some structural similarities to beta-blocking agents. Propafenone HCl occurs as colorless crystals or white crystalline powder with a very bitter taste. It is slightly soluble in water (20ºC), chloroform and ethanol. Propafenone extended release are capsules filled with granules containing the following inactive ingredients: ethylcellulose, lactose anhydrous, magnesium stearate and povidone. The capsules consist of D&C Red #28, FD&C Blue #1, FD&C Red #40, FD&C Yellow #5, FD&C Yellow #6, gelatin and titanium dioxide. In addition the ink consists of D&C Yellow #10 aluminum lake, iron oxide black, n-butyl alcohol, propylene glycol, FD&C Blue #2 aluminum lake, FD&C Red #40 aluminum lake, FD&C Blue #1 aluminum lake and shellac glaze~45% (20% esterfied) in ethanol.

CLINICAL PHARMACOLOGY

Mechanism of Action

Propafenone is a Class 1C antiarrhythmic drug with local anesthetic effects, and a direct stabilizing action on myocardial membranes. The electrophysiological effect of propafenone manifests itself in a reduction of upstroke velocity (Phase 0) of the monophasic action potential. In Purkinje fibers, and to a lesser extent myocardial fibers, propafenone reduces the fast inward current carried by sodium ions. Diastolic excitability threshold is increased and effective refractory period prolonged. Propafenone reduces spontaneous automaticity and depresses triggered activity.

Studies in anesthetized dogs and isolated organ preparations show that propafenone has beta-sympatholytic activity at about 1/50 the potency of propranolol. Clinical studies employing isoproterenol challenge and exercise testing after single doses of propafenone indicate a beta-adrenergic blocking potency (per mg) about 1/40 that of propranolol in man. In clinical trials with the immediate release formulation, resting heart rate decreases of about 8% were noted at the higher end of the therapeutic plasma concentration range. At very high concentrations in vitro, propafenone can inhibit the slow inward current carried by calcium, but this calcium antagonist effect probably does not contribute to antiarrhythmic efficacy. Moreover, propafenone inhibits a variety of cardiac potassium currents in in vitro studies (i.e. the transient outward, the delayed rectifier, and the inward rectifier current). Propafenone has local anesthetic activity approximately equal to procaine. Compared to propafenone, the main metabolite, 5-hydroxypropafenone, has similar sodium and calcium channel activity, but about 10 times less beta-blocking activity (N-depropylpropafenone has weaker sodium channel activity but equivalent affinity for beta-receptors).

Electrophysiology:

Electrophysiology studies in patients with ventricular tachycardia (VT) have shown that propafenone prolongs atrioventricular (AV) conduction while having little or no effect on sinus node function. Both atrioventricular (AV) nodal conduction time (AH interval) and His-Purkinje conduction time (HV interval) are prolonged. Propafenone has little or no effect on the atrial functional refractory period, but AV nodal functional and effective refractory periods are prolonged. In patients with Wolff-Parkinson-White (WPW) syndrome, propafenone hydrochloride immediate release tablets reduce conduction and increase the effective refractory period of the accessory pathway in both directions (see ADVERSE REACTIONS/ Electrocardiograms).

Hemodynamics:

Studies in humans have shown that propafenone exerts a negative inotropic effect on the myocardium. Cardiac catheterization studies in patients with moderately impaired ventricular function (mean C.I.=2.61 L/min/m2), utilizing intravenous propafenone infusions (loading dose of 2 mg/kg over 10 min+ followed by 2 mg/min for 30 min) that gave mean plasma concentrations of 3.0 mcg/mL (a dose that produces plasma levels of propafenone greater than does recommended oral dosing), showed significant increases in pulmonary capillary wedge pressure, systemic and pulmonary vascular resistances and depression of cardiac output and cardiac index.

Pharmacokinetics and Metabolism:

Absorption/Bioavailability

Maximal plasma levels of propafenone are reached between three to eight hours following the administration of propafenone hydrochloride extended release. Propafenone is known to undergo extensive and saturable presystemic biotransformation which results in a dose and dosage form dependent absolute bioavailability; e.g., a 150 mg immediate release tablet had an absolute bioavailability of 3.4%, while a 300 mg immediate release tablet had an absolute bioavailability of 10.6%. Absorption from a 300 mg solution dose was rapid, with an absolute bioavailability of 21.4%. At still larger doses, above those recommended, bioavailability of propafenone from immediate release tablets increased still further.

Relative bioavailability assessments have been performed between propafenone HCl ER capsules and propafenone HCl immediate release tablets. In extensive metabolizers, the bioavailability of propafenone from the SR formulation was less than that of the immediate release formulation as the more gradual release of propafenone from the prolonged-release preparations resulted in an increase in overall first pass metabolism (see Metabolism). As a result of the increased first pass effect, higher daily doses of propafenone were required from the SR formulation relative to the immediate release formulation, to obtain similar exposure to propafenone. The relative bioavailability of propafenone from the 325 twice daily regimens of propafenone ER approximates that of propafenone HCl immediate release 150 mg three times daily regimen. Mean exposure to 5-hydroxypropafenone was about 20-25% higher after SR capsule administration than after immediate-release tablet administration.

Food increased the exposure to propafenone 4-fold after single dose administration of 425 mg of propafenone HCl ER capsules. However, in the multiple dose study (425 mg dose BID), the difference between the fed and fasted state was not significant.

Distribution]

Following intravenous administration of propafenone, plasma levels decline in a bi-phasic manner consistent with a two compartment pharmacokinetic model. The average distribution half-life corresponding to the first phase was about five minutes. The volume of the central compartment was about 88 liters (1.1 L/kg) and the total volume of distribution about 252 liters.

In serum, propafenone is greater than 95% bound to proteins within the concentration range of 0.5 - 2 mcg/mL. Protein binding decreases to about 88% in patients with severe hepatic dysfunction.

Metabolism

There are two genetically determined patterns of propafenone metabolism. In over 90% of patients, the drug is rapidly and extensively metabolized with an elimination half-life from 2-10 hours. These patients metabolize propafenone into two active metabolites: 5-hydroxypropafenone which is formed by CYP2D6 and N-depropylpropafenone (norpropafenone) which is formed by both CYP3A4 and CYP1A2. In less than 10% of patients, metabolism of propafenone is slower because the 5-hydroxy metabolite is not formed or is minimally formed. In these patients, the estimated propafenone elimination half-life ranges from 10-32 hours. Decreased ability to form the 5-hydroxy metabolite of propafenone is associated with a diminished ability to metabolize debrisoquine and a variety of other drugs such as encainide, metoprolol, and dextromethorphan whose metabolism is mediated by the CYP2D6 isozyme. In these patients, the N-depropylpropafenone metabolite occurs in quantities comparable to the levels occurring in extensive metabolizers.

As a consequence of the observed differences in metabolism, administration of propafenone ER capsules to slow and extensive metabolizers results in significant differences in plasma concentrations of propafenone, with slow metabolizers achieving concentrations about twice those of the extensive metabolizers at daily doses of 850 mg/day. At low doses the differences are greater, with slow metabolizers attaining concentrations about three to four times higher than extensive metabolizers. In extensive metabolizers, saturation of the hydroxylation pathway (CYP2D6) results in greater-than-linear increases in plasma levels following administration of propafenone ER capsules. In slow metabolizers, propafenone pharmacokinetics are linear. Because the difference decreases at high doses and is mitigated by the lack of the active 5-hydroxy metabolite in the slow metabolizers, and because steady state conditions are achieved after four to five days of dosing in all patients, the recommended dosing regimen of propafenone ER capsules is the same for all patients. The large inter-subject variability in blood levels require that the dose of the drug be titrated carefully in patients with close attention paid to clinical and ECG evidence of toxicity (see DOSAGE AND ADMINISTRATION).

The 5-hydroxypropafenone and norpropafenone metabolites have electrophysiologic properties similar to propafenone in vitro. In man after administration of propafenone ER capsules, the 5-hydroxypropafenone metabolite is usually present in concentrations less than 40% of propafenone. The norpropafenone metabolite is usually present in concentrations less than 10% of propafenone.

Inter-Subject Variability

With propafenone, there is a considerable degree of inter-subject variability in pharmacokinetics which is due in large part to the first pass hepatic effect and non-linear pharmacokinetics in extensive metabolizers. A higher degree of inter-subject variability in pharmacokinetic parameters of propafenone was observed following both single and multiple dose administration of propafenone ER capsules. Inter-subject variability appears to be substantially less in the poor metabolizer group than in the extensive metabolizer group, suggesting that a large portion of the variability is intrinsic to CYP2D6 polymorphism rather than to the formulation.

The clearance of propafenone is reduced and the elimination half-life increased in patients with significant hepatic dysfunction (see PRECAUTIONS). Decreased liver function also increases the bioavailability of propafenone. Absolute bioavailability assessments have not been determined for the propafenone ER capsule formulation. Absolute bioavailability of propafenone HCl immediate release tablets has been demonstrated to be inversely related to indocyanine green clearance, reaching 60-70% at clearances of 7 mL/min and below.

Stereochemistry

Propafenone ER capsule is a racemic mixture. The R- and S-enantiomers of propafenone display stereoselective disposition characteristics. In vitro and in vivo studies have shown that the R-isomer of propafenone is cleared faster than the S-isomer via the 5-hydroxylation pathway (CYP2D6). This results in a higher ratio of S-propafenone to R-propafenone at steady state. Both enantiomers have equivalent potency to block sodium channels; however, the S-enantiomer is a more potent ß-antagonist than the R-enantiomer. Following administration of propafenone HCl immediate release tablets or propafenone ER capsules, the S/R ratio for the area under the plasma concentration-time curve was about 1.7. The S/R ratios of propafenone obtained after administration of 225, 325 and 425 mg propafenone ER capsules are independent of dose. In addition, no difference in the average values of the S/R ratios is evident between genotypes or over time.

Clinical Trials

Propafenone ER capsules has been evaluated in patients with a history of electrocardiographically documented recurrent episodes of symptomatic atrial fibrillation in two randomized, double-blind, placebo controlled trials.

RAFT]

In one U.S. multicenter study (propafenone ER capsules Atrial Fibrillation Trial, RAFT), three doses of propafenone ER capsules (225 mg BID, 325 mg BID and 425 mg BID) and placebo were compared in 523 patients with symptomatic, episodic atrial fibrillation. The patient population in this trial was 59% male with a mean age of 63 years, 91% White and 6% Black. The patients had a median history of atrial fibrillation of 13 months, and documented symptomatic atrial fibrillation within 12 months of study entry. Over 90% were NYHA Class I, and 21% had a prior electrical cardioversion. At baseline, 24% were treated with calcium channel blockers, 37% with beta blockers, and 38% with digoxin. Symptomatic arrhythmias after randomization were documented by transtelephonic electrocardiogram and centrally read and adjudicated by a blinded adverse event committee. Propafenone ER capsules administered for up to 39 weeks was shown to prolong significantly the time to the first recurrence of symptomatic atrial arrhythmia, predominantly atrial fibrillation, from Day 1 of randomization (primary efficacy variable) compared to placebo, as shown in Table 1.

Table 1: Analysis of tachycardia-free period (days) from Day 1 randomization
 | Propafenone HCl ER Dose
Parameter | 225 mg BID (N=126) n(%) | 325 mg BID (N=135) n(%) | 425 mg BID (N=136) n(%) | Placebo (N=126) n(%)
Patients completing with terminating event† | 66(52) | 56(41) | 41(30) | 87(69)
Comparison of tachycardia-free periods
Kaplan-Meier Median | 112 | 291 | * | 41
Range | 0-285 | 0-293 | 0-300 | 0-289
p-Value (Log-rank test) | 0.014 | <0.0001 | <0.0001 | --
Hazard Ratio compared to Placebo | 0.67 | 0.43 | 0.35 | --
95% CI for Hazard Ratio | (0.49,0.93) | (0.31,0.61) | (0.24,0.51) | --
* Fewer than 50% of the patients had events. The median time is not calculable.
† Terminating events comprised 91% atrial fibrillation, 5% atrial flutter, and 4% PSVT

There was a dose response for propafenone ER for the tachycardia-free period as shown in the proportional hazard analysis and the Kaplan-Meier curves presented in Figure 1.

In additional analyses, propafenone ER capsules (225 mg BID, 325 mg BID, and 425 mg BID) was also shown to prolong time to the first recurrence of symptomatic atrial fibrillation from Day 5 (steady state pharmacokinetics were attained). The antiarrhythmic effect of propafenone ER capsules was not influenced by age, gender, history of cardioversion, duration of atrial fibrillation, frequency of atrial fibrillation or use of medication that lowers heart rate. Similarly, the antiarrhythmic effect of propafenone ER capsules was not influenced by the individual use of calcium channel blockers, beta-blockers or digoxin. Too few non-White patients were enrolled to assess the influence of race on effects of propafenone ER capsules (propafenone hydrochloride).

No difference in the average heart rate during the first recurrence of symptomatic arrhythmia between propafenone ER capsules and placebo was observed.

ERAFT

In a European multicenter trial [(European Rythmonorm SR Atrial Fibrillation Trial (ERAFT)], two doses of propafenone ER capsules (325 mg BID and 425 mg BID) and placebo were compared in 293 patients. The patient population in this trial was 61% male, 100% White with a mean age of 61 years. Patients had a median duration of atrial fibrillation of 3.3 years, and 61% were taking medications that lowered heart rate. At baseline, 15% of the patients were treated with calcium channel blockers (verapamil and diltiazem), 42% with beta-blockers and 8% with digoxin. During a qualifying period of up to 28 days, patients had to have one ECG-documented incident of symptomatic atrial fibrillation. The double-blind treatment phase consisted of a four day loading period followed by a 91-day efficacy period. Symptomatic arrhythmias were documented by electrocardiogram monitoring.

In ERAFT, propafenone ER capsules were shown to prolong the time to the first recurrence of symptomatic atrial arrhythmia from Day 5 of randomization (primary efficacy analysis). The proportional hazard analysis revealed that both propafenone ER capsules doses were superior to placebo. The antiarrhythmic effect of propafenone ER was not influenced by age, gender, duration of atrial fibrillation, frequency of atrial fibrillation or use of medication that lowers heart rate. It was also not influenced by the individual use of calcium channel blockers, beta-blockers or digoxin. Too few non-White patients were enrolled to assess the influence of race on the effects of propafenone ER capsules. There was a slight increase in the incidence of centrally diagnosed asymptomatic atrial fibrillation or atrial flutter in each of the two propafenone ER capsules treatment groups compared to placebo.

INDICATIONS AND USAGE

Propafenone Extended Release Capsules are indicated to prolong the time to recurrence of symptomatic atrial fibrillation in patients without structural heart disease.

The use of propafenone ER capsules in patients with permanent atrial fibrillation or in patients exclusively with atrial flutter or PSVT has not been evaluated. Propafenone ER capsules should not be used to control ventricular rate during atrial fibrillation.

The effect of propafenone ER capsules on mortality has not been determined (see black box WARNINGS).

CONTRAINDICATIONS

Propafenone ER capsules are contraindicated in the presence of congestive heart failure, cardiogenic shock, sinoatrial, atrioventricular and intraventricular disorders of impulse generation or conduction (e.g., sick sinus node syndrome, atrioventricular block) in the absence of an artificial pacemaker, bradycardia, marked hypotension, bronchospastic disorders, electrolyte imbalance, or hypersensitivity to the drug.

WARNINGS

Mortality:

In the National Heart, Lung and Blood Institute’s Cardiac Arrhythmia Suppression Trial (CAST), a long-term, multi-center, randomized, double-blind study in patients with asymptomatic non-life-threatening ventricular arrhythmias who had a myocardial infarction more than six days but less than two years previously, an increased rate of death or reversed cardiac arrest rate (7.7%; 56/730) was seen in patients treated with encainide or flecainide (Class 1C antiarrhythmics) compared with that seen in patients assigned to placebo (3.0%; 22/725). The average duration of treatment with encainide or flecainide in this study was ten months.

The applicability of the CAST results to other populations (e.g., those without recent myocardial infarction) or other antiarrhythmic drugs is uncertain, but at present, it is prudent to consider any 1C antiarrhythmic to have a significant risk in patients with structural heart disease. Given the lack of any evidence that these drugs improve survival, antiarrhythmic agents should generally be avoided in patients with non-life-threatening ventricular arrhythmias, even if the patients are experiencing unpleasant, but not life-threatening, symptoms or signs.

Proarrhythmic Effects:

Propafenone has caused new or worsened arrhythmias. Such proarrhythmic effects include sudden death and life-threatening ventricular arrhythmias such as ventricular fibrillation, ventricular tachycardia, asystole and Torsade de Pointes. It may also worsen premature ventricular contractions or supraventricular arrhythmias, and it may prolong the QT interval. It is therefore essential that each patient given propafenone ER capsules be evaluated electrocardiographically prior to and during therapy, to determine whether the response to propafenone ER capsules supports continued treatment. Because propafenone prolongs the QRS interval in the electrocardiogram, changes in the QT interval are difficult to interpret.

In a 474 patient U.S. uncontrolled, open label multicenter trial using the immediate release formulation in patients with symptomatic SVT, 1.9% (9/474) of these patients experienced ventricular tachycardia (VT) or ventricular fibrillation (VF) during the study. However, in four of the nine patients, the ventricular tachycardia was of atrial origin. Six of the nine patients that developed ventricular arrhythmias did so within 14 days of onset of therapy. About 2.3% (11/474) of all patients had recurrence of SVT during the study which could have been a change in the patients’ arrhythmia behavior or could represent a proarrhythmic event. Case reports in patients treated with propafenone HCl for atrial fibrillation/flutter have included increased PVCs, VT, VF, Torsade de Pointes, asystole, and death.

In the RAFT study, there were five deaths, three in the pooled propafenone ER capsules group (0.8%) and two in the placebo group (1.6%). In the overall propafenone ER capsules and propafenone HCl immediate release database of eight studies, the mortality rate was 2.5% per year on propafenone HCl and 4% per year on placebo. Concurrent use of propafenone with other antiarrhythmic agents has not been well studied.

Use with Drugs that Prolong the QT Interval and Antiarrhythmic Agents:

The use of propafenone ER capsules (propafenone hydrochloride) in conjunction with other drugs that prolong the QT interval has not been extensively studied and is not recommended. Such drugs may include many antiarrhythmics, some phenothiazines, cisapride, bepridil, tricyclic antidepressants and oral macrolides. Class Ia and III antiarrhythmic agents should be withheld for at least five half-lives prior to dosing with propafenone ER capsules. The use of propafenone with Class Ia and III antiarrhythmic agents (including quinidine and amiodarone) is not recommended. There is only limited experience with the concomitant use of Class Ib or Ic antiarrhythmics.

Nonallergic Bronchospasm (e.g., chronic bronchitis, emphysema)

Patients with bronchospastic disease should not, in general, receive propafenone or other agents with beta-adrenergic-blocking activity.

Congestive Heart Failure

Propafenone exerts a negative inotropic activity on the myocardium as well as beta-blockade effects and may provoke overt congestive heart failure. In the U.S. trial (RAFT) in patients with symptomatic atrial fibrillation, congestive heart failure was reported in four (1%) patients receiving propafenone ER capsules (all doses), compared to one (0.8%) patient receiving placebo. Proarrhythmic effects are more likely to occur when propafenone is administered to patients with congestive heart failure (NYHA III and IV) or severe myocardial ischemia (see CONTRAINDICATIONS).

Conduction Disturbances:

Propafenone causes dose-related first degree AV block. Average PR interval prolongation and increases in QRS duration are also dose-related.

Propafenone should not be given to patients with atrioventricular and intraventricular conduction defects in the absence of a pacemaker (see CONTRAINDICATIONS).

In a U.S. trial (RAFT) in 523 patients with a history of symptomatic atrial fibrillation treated with propafenone ER capsules, electrocardiograms obtained in response to symptoms were associated with no patients having sinus rhythm with Mobitz Type I (Wenckenbach) second degree AV block, sinus rhythm with Mobitz Type II second degree AV block, or third degree AV block. Sinus bradycardia (rate <50 beats/min) was reported with the same frequency with propafenone ER capsules and placebo.

Effects on Pacemaker Threshold:

Propafenone may alter both pacing and sensing thresholds of artificial pacemakers. Pacemakers should be monitored and programmed accordingly during therapy.

Hematologic Disturbances:

Agranulocytosis (fever, chills, weakness, and neutropenia) has been reported in patients receiving propafenone. Generally, the agranulocytosis occurred within the first two months of propafenone therapy and upon discontinuation of therapy, the white count usually normalized by 14 days. Unexplained fever and/or decrease in white cell count, particularly during the initial three months of therapy, warrant consideration of possible agranulocytosis or granulocytopenia. Patients should be instructed to report promptly the development of any signs of infection such as fever, sore throat, or chills.

PRECAUTIONS

Hepatic Dysfunction

Propafenone is highly metabolized by the liver and should, therefore, be administered cautiously to patients with impaired hepatic function. Severe liver dysfunction increases the bioavailability of propafenone to approximately 70% compared to 3-40% in patients with normal liver function when given propafenone HCl immediate release tablets. In eight patients with moderate to severe liver disease administered propafenone HCl immediate release tablets, the mean half-life was approximately nine hours. No studies are currently available comparing bioavailability of propafenone from propafenone ER capsules in patients with normal and impaired hepatic function. Increased bioavailability of propafenone in these patients may result in excessive accumulation. Careful monitoring for excessive pharmacological effects (see OVERDOSAGE) should be performed for patients with impaired hepatic function.

Renal Dysfunction

Approximately 50% of propafenone metabolites are excreted in the urine following administration of propafenone HCl immediate release tablets. No studies have been performed to assess the percentage of metabolites eliminated in the urine following the administration of propafenone ER capsules.

Until further data are available, propafenone ER capsules should be administered cautiously to patients with impaired renal function. These patients should be carefully monitored for signs of overdosage (see OVERDOSAGE).

Information for Patients

Medications and Supplements:

Assessment of patients’ medication history should include all over-the-counter, prescription and herbal/natural preparations with emphasis on preparations that may affect the pharmacodynamics or kinetics of propafenone ER capsules (see WARNINGS/Use with Drugs that Prolong QT interval and Antiarrhythmic Agents). Patients should be instructed to notify their health care providers of any change in over-the-counter, prescription and supplement use. If a patient is hospitalized or is prescribed new medication for any condition, the patient must inform the health care provider of ongoing propafenone ER capsules therapy. Patients should also check with their health care providers prior to taking a new over-the-counter medicine.

Electrolyte Imbalance:

If patients experience symptoms that may be associated with altered electrolyte balance, such as excessive or prolonged diarrhea, sweating, vomiting, or loss of appetite or thirst, these conditions should be immediately reported to their health care provider.

Dosing Schedule:

Patients should be instructed NOT to double the next dose if a dose is missed. The next dose should be taken at the usual time.

Elevated ANA Titers:

Positive ANA titers have been reported in patients receiving propafenone. They have been reversible upon cessations of treatment and may disappear even in the face of continued propafenone therapy. These laboratory findings were usually not associated with clinical symptoms, but there is one published case of drug-induced lupus erythematosus (positive rechallenge); it resolved completely upon discontinuation of therapy. Patients who develop an abnormal ANA test should be carefully evaluated and, if persistent or worsening elevation of ANA titers is detected, consideration should be given to discontinuing therapy.

The 225 mg capsules contain FD&C Yellow No. 5 (tartrazine) which may cause allergic-type reactions (including bronchial asthma) in certain susceptible persons. Although the overall incidence of FD&C Yellow No.5 (tartrazine) sensitivity in the general population is low, it is frequently seen in patients who also have aspirin hypersensitivity.

Impaired Spermatogenesis:

Reversible disorders of spermatogenesis have been demonstrated in monkeys, dogs and rabbits after high dose intravenous administration of propafenone. Evaluation of the effects of short-term propafenone HCl administration on spermatogenesis in 11 normal subjects suggested that propafenone produced a reversible, short-term drop (within normal range) in sperm count. Subsequent evaluations in 11 patients receiving propafenone HCl chronically have found no effect of propafenone on sperm count.

Neuromuscular Dysfunction

Exacerbation of myasthenia gravis has been reported during propafenone HCl immediate release tablet therapy.

Drug Interactions

Propafenone is metabolized by CYP2D6 (major pathway) and CYP1A2 and CYP3A4. Drugs that inhibit CYP2D6 (such as desipramine, paroxetine, ritonavir, sertraline), CYP1A2 (such as amiodarone), and CYP3A4 (such as ketaconazole, ritonavir, saquinavir, erythromycin, and grapefruit juice) can be expected to cause increased plasma levels of propafenone. Appropriate monitoring is recommended when propafenone ER capsules are used together with such drugs. In addition, propafenone is an inhibitor of CYP2D6. Coadministration of propafenone with drugs metabolized by CYP2D6 (such as desipramine, imipramine, haloperidol, venlafaxine) might lead to increased plasma concentrations of these drugs. The effect of propafenone on the P-Glycoprotein transporter has not been studied.

Quinidine: Small doses of quinidine completely inhibit the CYP2D6 hydroxylation metabolic pathway, making all patients, in effect, slow metabolizers (see CLINICAL PHARMACOLOGY). Concomitant administration of quinidine (50 mg TID) with 150 mg immediate release propafenone TID decreased the clearance of propafenone by 60% in EM, making them PM. Steady state plasma concentrations increased by more than 2-fold for propafenone, and decreased 50% for 5-OH-propafenone. A 100 mg dose of quinidine increased steady state concentrations of propafenone 3-fold. Concomitant use of propafenone and quinidine is not recommended.

Digoxin:Concomitant use of propafenone and digoxin increased steady state serum digoxin exposure (AUC) in patients by 60 to 270%, and decreased the clearance of digoxin by 31 to 67%. Plasma digoxin levels of patients receiving propafenone should be monitored and digoxin dosage adjusted as needed.

Lidocaine: No significant effects on the pharmacokinetics of propafenone or lidocaine have been seen following their concomitant use in patients. However, concomitant use of propafenone and lidocaine have been reported to increase the risks of central nervous system side effects of lidocaine.

Beta-Antagonists: Concomitant use of propafenone and propranolol in healthy subjects increased propranolol plasma concentrations at steady state by 113%. In 4 patients, administration of metoprolol with propafenone increased the metoprolol plasma concentrations at steady state by 100-400%. The pharmacokinetics of propafenone was not affected by the coadministration of either propranolol or metoprolol. In clinical trials using propafenone immediate release tablets, patients who were receiving beta-blockers concurrently did not experience an increased incidence of side effects.

Warfarin: The concomitant administration of propafenone and warfarin increased warfarin plasma concentrations at steady state by 39% in healthy volunteers and prolonged the prothrombin time in patients taking warfarin. Adjustment of the warfarin dose should be guided by monitoring of the prothrombin time.

Cimetidine: Concomitant administration of propafenone immediate release tablets and cimetidine in 12 healthy subjects resulted in a 20% increase in steady state plasma concentrations of propafenone.

Rifampin: Concomitant administration of rifampin and propafenone in extensive metabolizers decreased the plasma concentrations of propafenone by 67% with a corresponding decrease of 5OH-propafenone by 65%. The concentrations of norpropafenone increased by 30%. In poor metabolizers, there was a 50% decrease in propafenone plasma concentrations and increased the AUC and Cmax of norpropafenone by 74 and 20%, respectively. Urinary excretion of propafenone and its metabolites decreased significantly. Similar results were noted in elderly patients: Both the AUC and Cmax propafenone decreased by 84%, with a corresponding decrease in AUC and Cmax of 5OH-propafenone by 69 and 57%.

Fluoxetine: Concomitant administration of propafenone and fluoxetine in extensive metabolizers increased the S propafenone Cmax and AUC by 39 and 50% and the R propafenone Cmax and AUC by 71 and 50%.

Amiodarone:Concomitant administration of propafenone and amiodarone can affect conduction and repolarization and is not recommended.

Post Marketing Reports:

Orlistat may limit the fraction of propafenone available for absorption. In post marketing reports, abrupt cessation of orlistat in patients stabilized on propafenone has resulted in severe adverse events including convulsions, atrioventricular block and acute circulatory failure.

Renal and Hepatic Toxicity in Animals:

Renal changes have been observed in the rat following six months of oral administration of propafenone HCl at doses of 180 and 360 mg/kg/day (about two and four times, respectively, the maximum recommended human daily dose [MRHD] on a mg/m² basis). Both inflammatory and non-inflammatory changes in the renal tubules, with accompanying interstitial nephritis, were observed. These changes were reversible, as they were not found in rats allowed to recover for six weeks. Fatty degenerative changes of the liver were found in rats following longer durations of administration of propafenone HCl at a dose of 270 mg/kg/day (about three times the MRHD on a mg/m² basis). There were no renal or hepatic changes at 90 mg/kg/day (equivalent to the MRHD on a mg/m² basis).

Carcinogenesis, Mutagenesis, Impairment of Fertility:

Lifetime maximally tolerated oral dose studies in mice (up to 360 mg/kg/day, about twice the maximum recommended human oral daily dose [MRHD] on a mg/m² basis) and rats (up to 270 mg/kg/day, about three times the MRHD on a mg/m² basis) provided no evidence of a carcinogenic potential for propafenone HCl.

Propafenone HCl tested negative for mutagenicity in the Ames (salmonella) test and in the in vivo mouse dominant lethal test. It tested negative for clastogenicity in the human lymphocyte chromosome aberration assay in vitro and in rat and Chinese hamster micronucleus tests, and other in vivo tests for chromosomal aberrations in rat bone marrow and Chinese hamster bone marrow and spermatogonia.

Propafenone HCl, administered intravenously to rabbits, dogs, and monkeys, has been shown to decrease spermatogenesis. These effects were reversible, were not found following oral dosing of propafenone HCl, were seen at lethal or near lethal dose levels and were not seen in rats treated either orally or intravenously (see PRECAUTIONS, Impaired Spermatogenesis). Treatment of male rabbits for 10 weeks prior to mating at an oral dose of 120 mg/kg/day (about 2.4 times the MRHD on a mg/m² basis) or an intravenous dose of 3.5 mg/kg/day (a spermatogenesis-impairing dose) did not result in evidence of impaired fertility. Nor was there evidence of impaired fertility when propafenone HCl was administered orally to male and female rats at dose levels up to 270 mg/kg/day (about 3 times the MRHD on a mg/m² basis).

Pregnancy

Teratogenic Effects: Pregnancy Category C. Propafenone HCl has been shown to be embryotoxic (decreased survival) in rabbits and rats when given in oral maternally toxic doses of 150 mg/kg/day (about three times the maximum recommended human dose [MRHD] on a mg/m² basis) and 600 mg/kg/day (about six times the MRHD on a mg/m² basis), respectively. Although maternally tolerated doses (up to 270 mg/kg/day, about three times the MRHD on a mg/m² basis) produced no evidence of embryotoxicity in rats, post-implantation loss was elevated in all rabbit treatment groups (doses as low as 15 mg/kg/day, about 1/3 the MRHD on a mg/m² basis). There are no adequate and well-controlled studies in pregnant women. Propafenone ER capsules (propafenone hydrochloride) should be used during pregnancy only if the potential benefit justifies the potential risk to the fetus.

Non-Teratogenic Effects: In a study in which female rats received daily oral doses of propafenone HCl from mid-gestation through weaning of their offspring, doses as low as 90 mg/kg/day (equivalent to the MRHD on a mg/m² basis) produced increases in maternal deaths. Doses of 360 or more mg/kg/day (four or more times the MRHD on a mg/m² basis) resulted in reductions in neonatal survival, body weight gain and physiological development.

Labor and Delivery

It is not known whether the use of propafenone during labor or delivery has immediate or delayed adverse effects on the fetus, or whether it prolongs the duration of labor or increases the need for forceps delivery or other obstetrical intervention.

Nursing Mothers

Propafenone is excreted in human milk. Caution should be exercised when propafenone ER capsules are administered to a nursing mother.

Pediatric Use

The safety and effectiveness of propafenone in pediatric patients have not been established.

Geriatric Use

Of the total number of subjects in Phase III clinical studies of propafenone ER capsules (propafenone hydrochloride) 45.7 percent were 65 and over, while 15.7 percent were 75 and over. No overall differences in safety or effectiveness were observed between these subjects and younger subjects, but greater sensitivity of some older individuals at higher doses cannot be ruled out. The effect of age on the pharmacokinetics and pharmacodynamics of propafenone has not been studied.

ADVERSE REACTIONS

The data described below reflect exposure to propafenone ER capsules 225 mg BID in 126 patients, to propafenone ER capsules 325 mg BID in 135 patients, to propafenone ER capsules 425 mg BID in 136 patients, and to placebo in 126 patients for up to 39 weeks in a placebo-controlled trial (RAFT) conducted in the U.S. The most commonly reported adverse events in the trial included dizziness, chest pain, palpitations, taste disturbance, dyspnea, nausea, constipation, anxiety, fatigue, upper respiratory tract infection, influenza, first degree heart block and vomiting. The frequency of discontinuation due to adverse events was highest during the first 14 days of treatment. The majority of the patients with serious adverse events who withdrew or were discontinued recovered without sequelae.

Adverse events occurring in 2% or more of the patients in any of the RAFT propafenone ER capsules treatment groups and more common with propafenone than with placebo, excluding those that are common in the population and those not plausibly related to drug therapy, are listed in Table 2.

Table 2: Most common adverse events (≥2% in any RAFT propafenone ER treatment group and more common on propafenone than on placebo)
Propafenone ER Capsules
MeDRA Body System/Preferred Term | 225 mg BID (N = 126) n (%) | 325 mg BID (N = 135) n (%) |  | 425 mg BID (N = 136) n (%) | Placebo (N=126 n (%)
Mean exposure (days) | 124 | 149 |  | 141 | 91
Cardiac disorders
Angina pectoris | 0 (0) | 0 (0) |  | 3 (2) | 0 (0)
Atrial flutter | 3 (2) | 2 (1) |  | 0 (0) | 1 (1)
AV block first degree | 3 (2) | 3 (2) |  | 4 (3) | 0 (0)
Bradycardia | 4 (3) | 4 (3) |  | 6 (4) | 1 (1)
Cardiac failure congestive | 0 (0) | 1 (1) |  | 3 (2) | 1 (1)
Cardiac murmur | 2 (2) | 3 (2) |  | 6 (4) | 0 (0)
Edema | 6 (5) | 18 (13) |  | 10 (7) | 8 (6)
Eye disorders
Vision blurred | 1 (1) | 1 (1) |  | 5 (4) | 0 (0)
Gastrointestinal disorders
Constipation | 10 (8) | 19 (14) |  | 16 (12) | 3 (2)
Diarrhea | 2 (2) | 3 (2) |  | 5 (4) | 3 (2)
Dry mouth | 1 (1) | 1 (1) |  | 5 (4) | 1 (1)
Flatulence | 3 (2) | 3 (2) |  | 1 (1) | 0 (0)
Nausea | 11 (9) | 15 (11) |  | 23 (17) | 11 (9)
Vomiting | 1 (1) | 0 (0) |  | 8 (6) | 3 (2)
General disorder and administration site
Fatigue | 14 (11) | 17 (13) | 17 (13) |  | 7 (6)
Weakness | 4 (3) | 6 (4) | 6 (4) |  | 3 (2)
Infections and Infestations
Upper respiratory tract infection | 11 (9) | 16 (12) | 11 (8)) |  | 7 (6)
Investigations
Blood alkaline phosphatase increased | 0 (0) | 0 (0) | 4 (3) |  | 0 (0)
Cardioactive drug level above therapeutic | 1 (1) | 1 (1) | 3 (2) |  | 1 (1)
Hematuria | 2 (2) | 2 (1) | 4 (3) |  | 3 (2)
Musculoskeletal, connective tissue and bone
Muscle weakness | 1 (1) | 5 (4) | 1 (1) |  | 0 (0)
Nervous system disorders
Dizziness (excluding vertigo) | 29 (23) | 28 (21) | 29 (21) |  | 18 (14)
Headache | 8 (6) | 12 (9) | 14 (10) |  | 11 (9)
Taste disturbance | 7 (6) | 18 (13) | 30 (22) |  | 1 (1)
Tremor | 2 (2) | 0 (0) | 3 (2) |  | 1 (1)
Somnolence | 1 (1) | 1 (1) | 4 (3) |  | 0 (0)
Psychiatric disorders
Anxiety | 12 (10) | 17 (13) | 16 (12) |  | 13 (10)
Depression | 1 (1) | 4 (3) | 0 (0) |  | 2 (2)
Respiratory, thoracic and mediastinal disorder
Dyspnea | 16 (13) | 23 (17) | 17 (13) |  | 9 (7)
Rales | 2 (2) | 1 (1) | 3 (2) |  | 0 (0)
Wheezing | 0 (0) | 0 (0) | 3 (2) |  | 0 (0)
Skin & subcutaneous tissue disorders
Ecchymosis | 2 (2) | 3 (2) | 5 (4) |  | 0 (0)

No clinically important differences in incidence of adverse reactions were noted by age, or gender. Too few non-White patients were enrolled to assess adverse events according to race. Adverse events occurring in 2% or more of the patients in any of the ERAFT propafenone ER treatment groups and not listed in Table 2 include the following: bundle branch block left, bundle branch block right, conduction disorders, sinus bradycardia and hypotension.

Other adverse events reported with propafenone clinical trials not already listed in Table 2 include the following adverse events by body and preferred term.

Blood and lymphatic system disorders: anemia; lymphadenopathy; spleen disorder; thrombocytopenia; Cardiac disorders: angina unstable; arrhythmia; atrial hypertrophy; atrioventricular block; bundle branch block left; bundle branch block right; cardiac arrest; cardiac disorder; conduction disorder; coronary artery disease; extrasystoles; myocardial infarction; nodal arrhythmia; palpitations; pericarditis; sinoatrial block; sinus arrest; sinus arrhythmia; sinus bradycardia; supraventricular extrasystoles; supraventricular tachycardia; ventricular arrhythmia; ventricular extrasystoles; ventricular hypertrophy; Ear and labyrinth disorders: hearing impaired; tinnitus; vertigo; Eye disorders: eye hemorrhage; eye inflammation; eyelid ptosis; miosis; retinal disorder; visual acuity reduced; Gastrointestinal disorders: abdominal distension; abdominal pain; dry throat; duodenitis; dyspepsia; dysphagia; eructation; gastritis; gastroesophageal reflux disease; gingival bleeding; glossitis; glossodynia; gum pain; halitosis; intestinal obstruction; melena; mouth ulceration; pancreatitis; peptic ulcer; rectal bleeding; sore throat; General disorders and administration site conditions: chest pain; feeling hot; hemorrhage; malaise; pain; pyrexia; Hepato-biliary disorders: hepatomegaly; Investigations: abnormal electrocardiogram; abnormal heart sounds; abnormal liver function tests; abnormal pulse; carotid bruit; decreased blood chloride; decreased blood pressure; decreased blood sodium; decreased hemoglobin; decreased neutrophil count; decreased platelet count; decreased prothrombin level; decreased red blood cell count; decreased weight; electrocardiogram QT prolonged; glycosuria present; heart rate irregular; increased alanine aminotransferase; increased aspartate aminotransferase; increased blood bilirubin; increased blood cholesterol; increased blood creatinine; increased blood glucose; increased blood lactate dehydrogenase; increased blood pressure; increased blood prolactin; increased blood triglycerides; increased blood urea; increased blood uric acid; increased eosinophil count; increased gamma-glutamyltransferase; increased monocyte count; increased prostatic specific antigen; increased prothrombin level; increased weight; increased white blood cell count; ketonuria present; proteinuria present; Metabolism and nutrition disorders: anorexia; dehydration; diabetes mellitus; gout; hypercholesterolemia; hyperglycemia; hyperlipidemia; hypokalemia; Musculoskeletal, connective tissue and bone disorders: arthritis; bursitis; collagen-vascular disease; costochondritis; joint disorder; muscle cramps; muscle spasms; myalgia; neck pain; pain in jaw; sciatica; tendonitis; Nervous system disorders: amnesia; ataxia; balance impaired; brain damage; cerebrovascular accident; dementia; gait abnormal; hypertonia; hypothesia; insomnia; paralysis; paresthesia; peripheral neuropathy; speech disorder; syncope; tongue hypoesthesia; Psychiatric disorders: decreased libido; emotional disturbance; mental disorder; neurosis; nightmare; sleep disorder; Renal and urinary disorders: dysuria; nocturia; oliguria; pyuria; renal failure; urinary casts; urinary frequency; urinary incontinence; urinary retention; urine abnormal; Reproductive system and breast disorders: breast pain; impotence; prostatism; Respiratory, thoracic and mediastinal disorders: atelectasis; breath sounds decreased; chronic obstructive airways disease; cough; epistaxis; hemoptysis; lung disorder; pleural effusion; pulmonary congestion; rales; respiratory failure; rhinitis; throat tightness; Skin and subcutaneous tissue disorders: alopecia; dermatitis; dry skin; erythema; nail abnormality; petechiae; pruritis; sweating increased; urticaria; Vascular disorders: arterial embolism limb; deep limb venous thrombosis; flushing; hematoma; hypertension; hypertensive crisis; hypotension; labile blood pressure; pallor; peripheral coldness; peripheral vascular disease; thrombosis.

Laboratory: Electrocardiograms

Propafenone prolongs the PR and QRS intervals in patients with atrial and ventricular arrhythmias. Prolongation of the QRS interval makes it difficult to interpret the effect of propafenone on the QT interval.

Table 3: Mean Change in 12-Lead Electrocardiogram Results (RAFT)
 | Propafenone ER Capsules BID dosing
 | 225 mg | 325 mg | 425 mg | Placebo
 | n=126 | n=135 | n=136 | n=126
PR (ms) | 9±22 | 12±23 | 21±24 | 1±16
QRS (ms) | 4±14 | 6±15 | 6±15 | -2±12
QTc* (ms) | 2±30 | 5±36 | 6±37 | 5±35
*Calculated using Bazett’s correction factor.

In RAFT, the distribution of the maximum changes in QTc compared to baseline over the study in each patient was similar in the propafenone ER capsules 225 mg BID, 325 mg BID, and 425 mg BID and placebo dose groups. Similar results were seen in the ERAFT study.

Table 4: Number of patients according to the range of maximum QTc change compared to baseline over the study in each dose group (RAFT study)
Range of maximum QTc change | Propafenone ER Capsules |  |  | Placebo
 | 225 mg BID | 325 mg BID | 425 mg BID
 | N=119 | N=129 | N=123 | N=100
 | n (%) | n (%) | n (%) | n (%)
>20% | 1 (1%) | 6 (5%) | 3 (2%) | 5 (4%)
10-20% | 19 (16%) | 28 (22%) | 32 (26%) | 24 (20%)
≤10% | 99 (83%) | 95 (74%) | 88 (72%) | 91 (76%)

OVERDOSAGE

The symptoms of overdosage may include hypotension, somnolence, bradycardia, intra-atrial and intraventricular conduction disturbances, and rarely convulsions and high grade ventricular arrhythmias. Defibrillation as well as infusion of dopamine and isoproterenol have been effective in controlling abnormal ventricular rhythm and blood pressure. Convulsions have been alleviated with intravenous diazepam. General supportive measures such as mechanical respiratory assistance and external cardiac massage may be necessary.

The hemodialysis of propafenone in patients with an overdose is expected to be of limited value in the removal of propafenone as a result of both its high protein binding (>95%) and large volume of distribution.

DOSAGE AND ADMINISTRATION

The dose of propafenone ER capsules must be individually titrated on the basis of response and tolerance. Therapy should be initiated with propafenone ER capsules 225 mg given every twelve hours. Dosage may be increased at a minimum of five day interval to 325 mg given every twelve hours. If additional therapeutic effect is needed, the dose of propafenone ER capsules may be increased to 425 mg given every twelve hours.

In patients with hepatic impairment or having significant widening of the QRS complex or second or third degree AV block, dose reduction should be considered.

Propafenone ER capsules can be taken with or without food. Do not crush or further divide the contents of the capsule.

HOW SUPPLIED

Propafenone Extended Release Capsules, 325 mg are available as hard gelatin capsules containing 325 mg of propafenone HCl. The capsule is an orange opaque cap printed “par/210” in black ink and white opaque body printed “par/210” in black ink.

NDC 49884-210-02 Bottles of 60 capsules

NDC 49884-210-01 Bottles of 100 capsules

NDC 49884-210-05 Bottles of 500 capsules

NDC 49884-210-10 Bottles of 1000 capsules

Storage: Store at 25°C (77°F); excursions permitted to 15-30°C (59-86°F) [see USP Controlled Room Temperature]. Dispense in a tight container as defined in the USP.

Manufactured by:

Par Pharmaceutical Companies, Inc.

Spring Valley, NY 10977

I03/10

Repackaged by:

Rebel Distributors Corp

Thousand Oaks, CA 91320